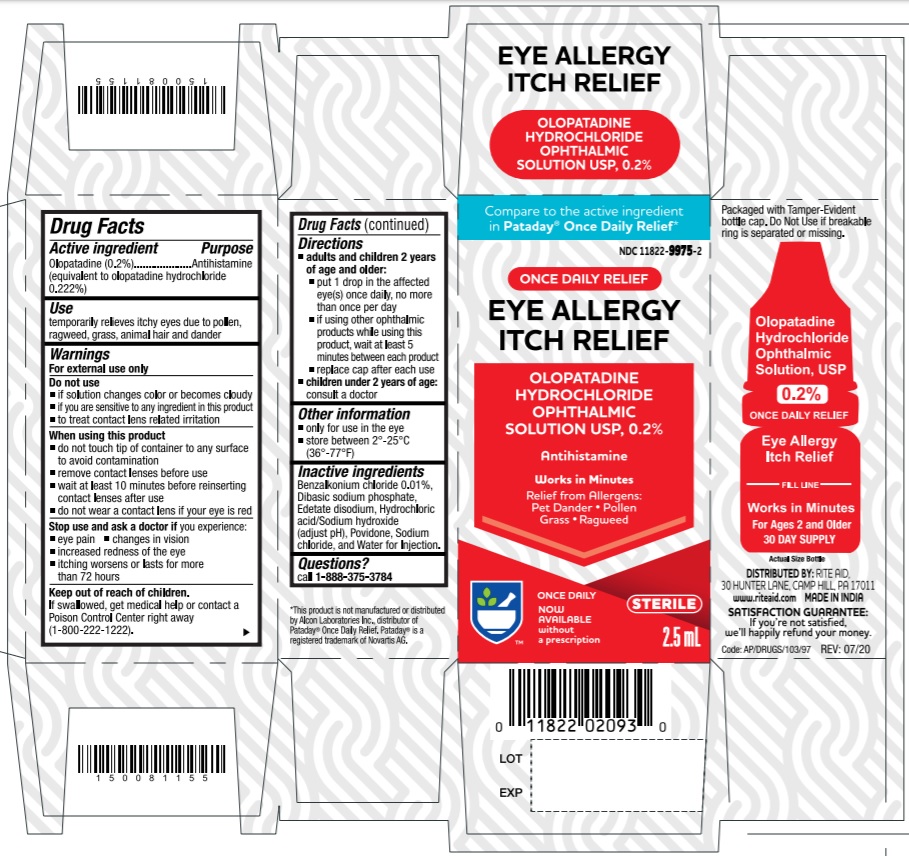 DRUG LABEL: Olopatadine Hydrochloride Ophthalmic Solution
NDC: 11822-9975 | Form: SOLUTION
Manufacturer: Rite Aid Corporation
Category: otc | Type: Human OTC Drug Label
Date: 20251212

ACTIVE INGREDIENTS: OLOPATADINE HYDROCHLORIDE 2 mg/1 mL
INACTIVE INGREDIENTS: BENZALKONIUM CHLORIDE; SODIUM PHOSPHATE, DIBASIC, ANHYDROUS; EDETATE DISODIUM; HYDROCHLORIC ACID; POVIDONE K30; SODIUM CHLORIDE; SODIUM HYDROXIDE; WATER

ACTIVE INGREDIENT

Olopatadine (0.2%) (equivalent to olopatadine hydrochloride 0.222%)

PURPOSE

Antihistamine

USE

temporarily relieves itchy eyes due to pollen, ragweed, grass, animal hair and dander

WARNINGS

For external use only

DO NOT USE

- if solution changes color or becomes cloudy
- if you are sensitive to any ingredient in this product
- to treat contact lens related irritation

WHEN USING THIS PRODUCT

- do not touch tip of container to any surface to avoid contamination
- remove contact lenses before use
- wait at least 10 minutes before reinserting contact lenses after use
- do not wear a contact lens if your eye is red

STOP USE AND ASK DOCTOR IF

you experience:

- eye pain
- changes in vision
- increased redness of the eye
- itching worsens or lasts for more than 72 hours

KEEP OUT OF REACH OF CHILDREN

If swallowed, get medical help or contact a Poison Control Center right away.

DIRECTIONS

- adults and children 2 years of age and older:
- put 1 drop in the affected eye(s) once daily, no more than once per day
- if using other ophthalmic products while using this product, wait at least 5 minutes between each product
- replace cap after each use
- children under 2 years of age: consult a doctor

OTHER INFORMATION

• only for use in the eye
• store between 2° to 25°C (36° to 77°F)

INACTIVE INGREDIENTS

Benzalkonium chloride 0.01%, Dibasic sodium phosphate, Edetate disodium, Hydrochloric acid/Sodium hydroxide (adjust pH), Povidone, Sodium chloride, and Water for Injection.

QUESTIONS?

Call 1-888-375-3784